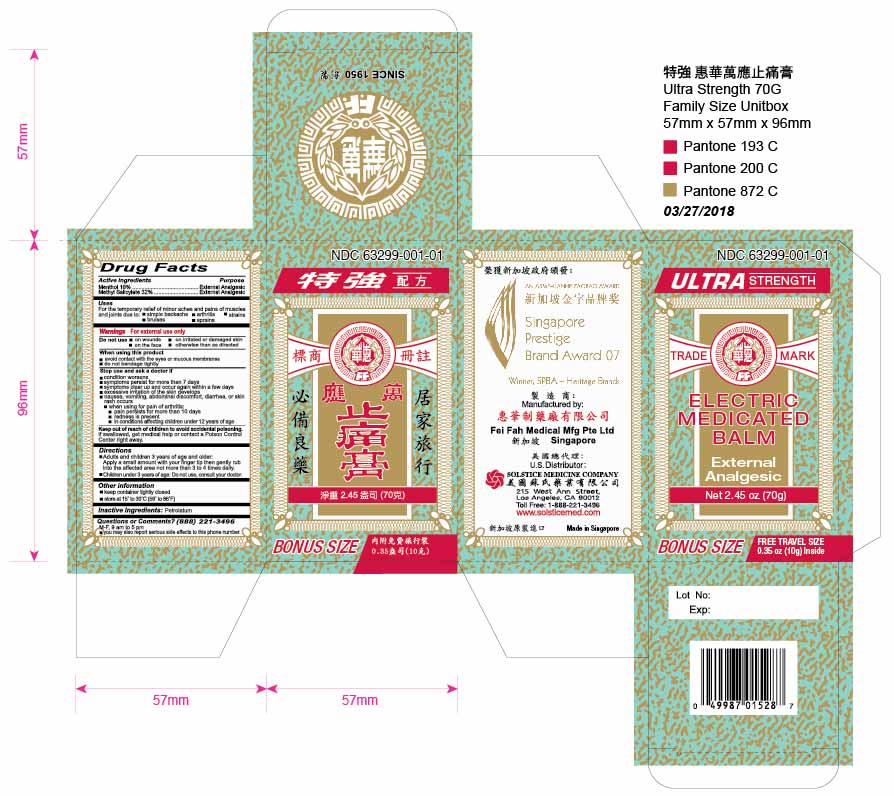 DRUG LABEL: MENTHOL AND METHYL SALICYLATE
NDC: 63299-001 | Form: OINTMENT
Manufacturer: FEI FAH MEDICAL MANUFACTURING PTE LTD
Category: otc | Type: HUMAN OTC DRUG LABEL
Date: 20251110

ACTIVE INGREDIENTS: MENTHOL 16 g/100 g; METHYL SALICYLATE 32 g/100 g
INACTIVE INGREDIENTS: PETROLATUM

DRUG FACTS

Active ingredients
Menthol 16%
Methyl salicylate 32%

Purpose
External analgesic
External analgesic

Uses
For the temporary relief of minor aches and pains of muscles and joints due to
simple backache
arthritis
strains
bruises
sprains

Warnings
For external use only

Do not use
on wounds
on irritated or damaged skin
on the face
otherwise than as directed

When using this product
avoid contact with the eyes or mucous membranes
do not bandage tightly

Stop use and ask a doctor if
condition worsens
symptoms persist for more than 7 days
symptoms clear up and occur again within a few days
excessive irritation of the skin develops
nausea, vomiting, abdominal discomfort, diarrhea, or skin rash occurs
when using for pain of arthritis
pain persists for more than 10 days
redness is present
in conditions affecting children under 12 years of age

Keep out of reach of children to avoid accidental poisoning
If swallowed, get medical help or contact a Poison Control Center right away.

Directions
Adults and children 3 years of age and older: Apply a small amount with your finger tip then gently rub into the affected area not more than 3 to 4 times daily.
Children under 3 years of age: Do not use, consult your doctor.

Other information
keep container tightly closed
store at 15° to 30°C (59° to 86°F)

Inactive ingredients
Petrolatum

Questions or comments? (888) 221-3496 M-F 9am to 5pm
you may also report serious side effects to this phone number

PACKAGE LABEL

ELECTRIC MEDICATED BALM
External Analgesic
NDC 63299-001-01
NET 2.45 oz (70g)